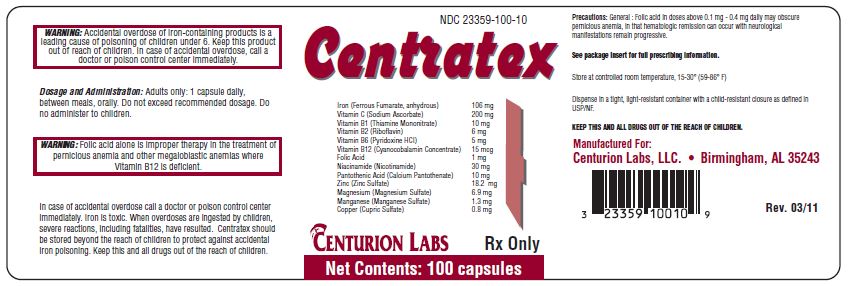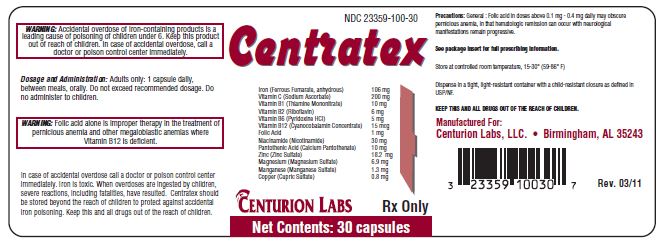 DRUG LABEL: Centratex
NDC: 23359-100 | Form: CAPSULE
Manufacturer: Centurion Labs, LLC
Category: prescription | Type: HUMAN PRESCRIPTION DRUG LABEL
Date: 20240131

ACTIVE INGREDIENTS: IRON 106 mg/1 1; SODIUM ASCORBATE 200 mg/1 1; THIAMINE MONONITRATE 10 mg/1 1; RIBOFLAVIN 6 mg/1 1; PYRIDOXINE HYDROCHLORIDE 5 mg/1 1; FOLIC ACID 1 mg/1 1; CYANOCOBALAMIN 15 ug/1 1; NIACINAMIDE 30 mg/1 1; CALCIUM PANTOTHENATE 10 mg/1 1; ZINC SULFATE 18.2 mg/1 1; MAGNESIUM SULFATE, UNSPECIFIED 6.9 mg/1 1; MANGANESE SULFATE 1.3 mg/1 1; CUPRIC SULFATE ANHYDROUS 0.8 mg/1 1
INACTIVE INGREDIENTS: CELLULOSE, MICROCRYSTALLINE; SILICON DIOXIDE; MAGNESIUM STEARATE; GELATIN

Centratex
Capsules

Capsules

Iron 106 mg, Sodium Ascorbate 200 mg, Thiamine 10 mg, Riboflavin 6 mg, Pyridoxine 5 mg, Folic Acid 1 mg, Cyanocobalamin 15 mcg, Niacinamide 30 mg, Pantothenic Acid 10 mg, Zinc 18.2 mg, Magnesium 6.9 mg

Copper (Copper sulfate) | 0.8 mg
Manganese (Manganese Sulfate) | 1.3 mg

A medical food, for use only under the direction and supervision of a licensed physician.

RX only

DESCRIPTION

Active Ingredients (Each capsule)

Ferrous Fumerate | 106 mg(Iron)
Vitamin C (Sodium Ascorbate) | 200 mg
Vitamin B1 (Thiamine Mononitrate) | 10 mg
Vitamin B2 (Riboflavin) | 6 mg
Vitamin B6 (Pyridoxine HCL) | 5 mg
Folic Acid | 1 mg
Vitamin B12 | 15 mcg
Niacinamide | 30 mg
Pantothenic Acid | 10 mg
Zinc (Zinc Sulfate) | 18.2 mg
Magnesium (Magnesium Sulfate) | 6.9 mg
Copper (Copper Sulfate) | 0.8 mg
Manganese (Manganese Sulfate) | 1.3 mg

Inactive Ingredients

Microcrystalline Cellulose, Silica, Magnesium Stearate, Gelatin Capsule

INDICATIONS

For the treatment of anemia due to lack of iron and low folate as in menorrhagia, pregnancy, puberty, excessive blood loss, and advanced age. Also for treatment of conditions where iron and vitamin C deficiency occur together, along with a poor intake or increased need for B-complex vitamins in chronic and acute illness, as well as cases of metabolic stress, and in periods of extended recovery.

CONTRAINDICATIONS

Centratex is contraindicated in patients with a known hypersensitivity to any of its ingredients. Iron compounds are contraindicated in patients with hemosiderosis, hemochromatosis, and hemolytic anemias. Folic acid may obscure signs and symptoms of pernicious anemia and is therefore a contraindication as well.

Warning

Accidental overdose of iron-containing products is a leading cause of fatal poisoning in children under 6. Keep this product out of reach of children. In case of accidental overdose, call a doctor or poison control center immediately. Iron is toxic and has been shown to cause severe reactions in children including death.

Warning

Folic acid alone is improper therapy in the treatment of pernicious anemia and other megaloblastic anemias where vitamin B-12 is deficient.

PRECAUTIONS

General

Folic acid in doses above 0.1 mg – 0.4 mg daily may obscure pernicious anemia, in that hematologic remission can occur while neurological manifestations remain progressive.

PEDIATRIC USE

Safety and effectiveness in pediatric patients has not been established.

GERIATRIC USE

No clinical studies have been performed in patients over 65 to determine whether older persons respond differently from younger persons. Physicians should consider that elderly persons may have decreased hepatic, renal, or cardiac function.

ADVERSE REACTION

Allergic sensitizations have been reported following both oral and parenteral administration of folic acid. Gastrointestinal disturbances (anorexia, nausea, diarrhea, constipation) occur occasionally, but are usually mild and subside with continuation of therapy and physician encouragement. Although the absorption of iron is best when taken between meals, occasional G.I. disturbances may be controlled by giving Centratex shortly after meals.

DOSAGE AND ADMINISTRATION

Adults only: 1 capsule daily between meals, orally. Not recommended in children.

HOW SUPPLIED

Centratex is supplied as a natural gelatin capsule with tan speckled powder. Centratex is available in bottles of 100 (NDC 23359-100-10) and bottles of 30 (NDC 23359-100-30) Dispense in a tight, light resistant container as defined in the USP/NF with a child resistant closure. Store at room temperature between 15-30 degrees C (59-86 degrees F) Keep in a cool, dry place.

RX ONLY

Centurion Labs, LLC
Birmingham, AL 35243

Rev. 8/17

PRINCIPAL DISPLAY PANEL - 30 Capsule Bottle Lable

NDC 23359-100-30

Centratex

Iron (Ferrous Fumarate, anhydrous | 106 mg
Vitamin C (Sodium Ascorbate) | 200 mg
Vitamin B1 (Thiamine Mononitrate) | 10 mg
Vitamin B2 (Riboflavin) | 6 mg
Vitamin B6 (Pyridoxine HCl) | 5 mg
Vitamin B12 (Cyanocobalamin Concentrate) | 15 mcg
Folic Acid | 1 mg
Niacinamide (Nicotinamide) | 30 mg
Pantothenic Acid (Calcium Pantothenate) | 10 mg
Zinc (Zinc Sulfate) | 18.2 mg
Magnesium (Magnesium Sulfate) | 6.9 mg
Manganese (Manganese Sulfate) | 1.3 mg
Copper (Cupric Sulfate) | 0.8 mg

CENTURION LABS Rx Only

Net Contents: 30 capsules

PRINCIPAL DISPLAY PANEL - 100 Capsule Bottle Label

NDC 23359-100-10

Centratex

Iron (Ferrous Fumarate, anhydrous) | 106 mg
Vitamin C (Sodium Ascorbate) | 200 mg
Vitamin B1 (Thiamine Mononitrate) | 10 mg
Vitamin B2 (Riboflavin) | 6 mg
Vitamin B6 (Pyridoxine HCl) | 5 mg
Vitamin B12 (Cyanocobalamin Concentrate) | 15 mcg
Folic Acid | 1 mg
Niacinamide (Nicotinamide) | 30 mg
Pantothenic Acid (Calcium Pantothenate) | 10 mg
Zinc (Zinc Sulfate) | 18.2 mg
Magnesium (Magnesium Sulfate) | 6.9 mg
Manganese (Manganese Sulfate) | 1.3 mg
Copper (Copper Sulfate) | 0.8 mg

CENTURION LABS
Rx Only

Net Contents: 100 capsules